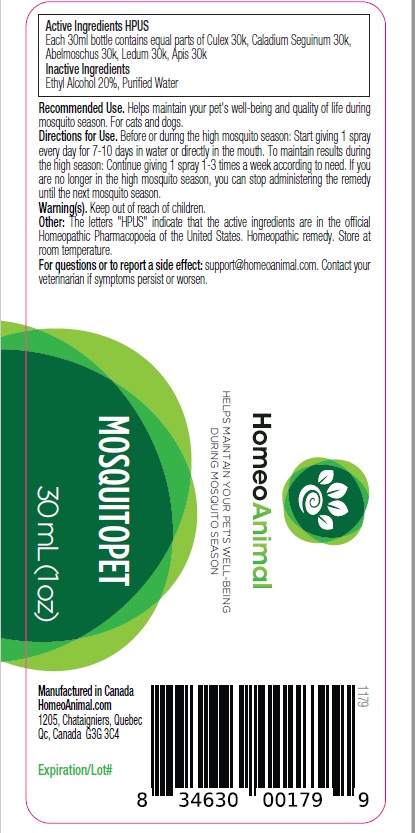 DRUG LABEL: MOSQUITOPET
NDC: 86147-055 | Form: LIQUID
Manufacturer: Groupe Cyrenne Inc.
Category: homeopathic | Type: OTC ANIMAL DRUG LABEL
Date: 20230419

ACTIVE INGREDIENTS: CULEX PIPIENS 200 [kp_C]/30 mL; DIEFFENBACHIA SEGUINE WHOLE 200 [kp_C]/30 mL; ABELMOSCHUS MOSCHATUS SEED 30 [kp_C]/30 mL; APIS MELLIFERA 30 [kp_C]/30 mL; RHODODENDRON TOMENTOSUM LEAFY TWIG 30 [kp_C]/30 mL
INACTIVE INGREDIENTS: ALCOHOL; WATER

Active ingredients

Culex 200k, Caladium Seguinum 200k, Abelmoschus 30k, Ledum 30k, Apis 30k

Uses

Helps maintain your pet's well-being and quality of life during mosquito season. For cats and dogs.

Warnings

Shake well before use. Respect the dosage. Keep out of reach of children.

Direction

Before or during the high mosquito season: Start giving 1 spray every day for 7-10 days in water or directly in the mouth. To maintain results during the high season: Continue giving 1 spray 1-3 times a week according to need. If you are no longer in the high mosquito season, you can stop administering the remedy until the next mosquito season.

Inactive ingredients

Ethyl alcohol 20%, purified water

Other information

The letters "HPUS" indicate that the active ingredients are in the official Homeopathic Pharmacopoeia of the United States. Homeopathic remedy. Store at room temperature.